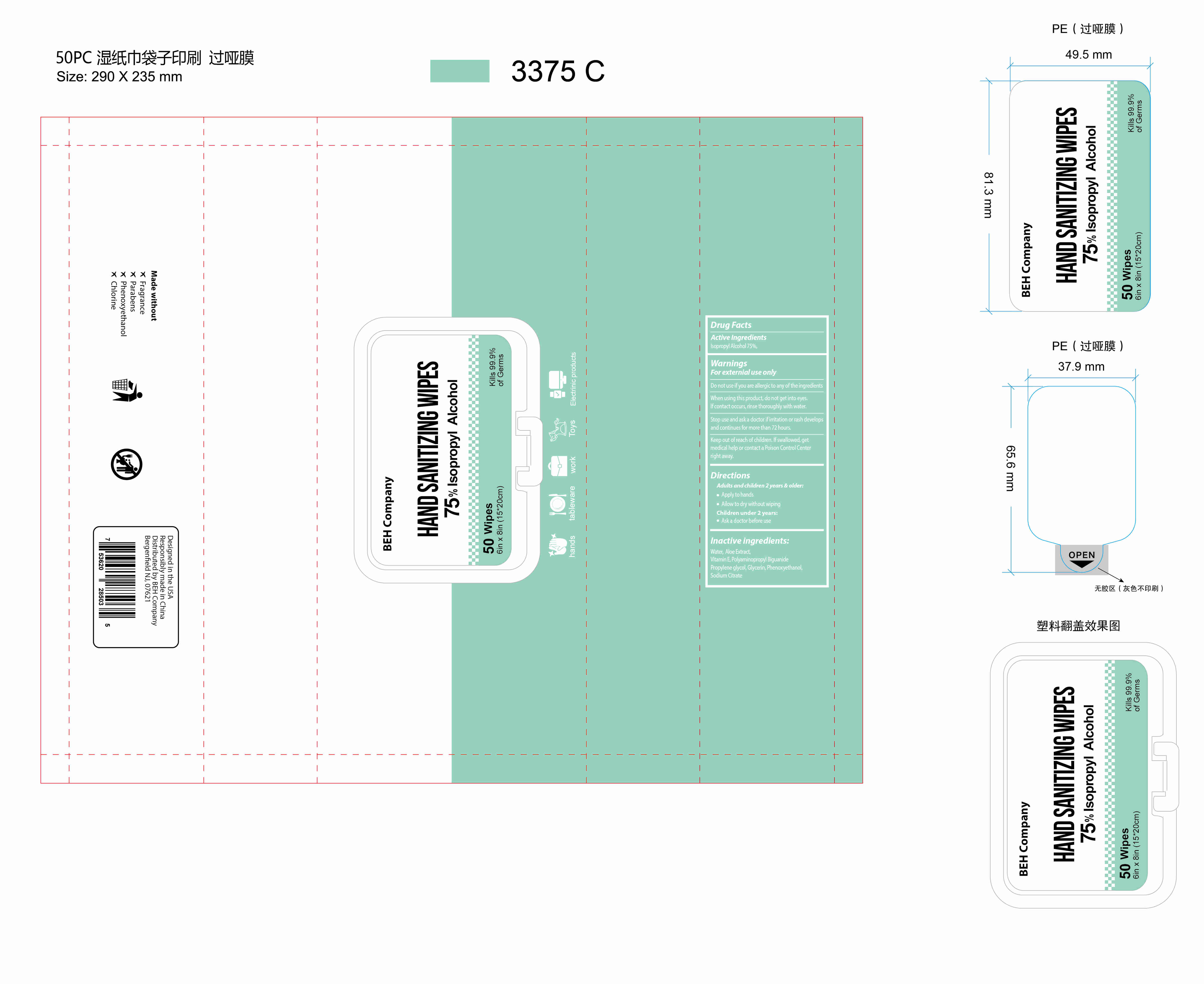 DRUG LABEL: Hand Sanitizer Wipes
NDC: 54237-060 | Form: CLOTH
Manufacturer: Guangzhou Daieme Cosmetic Co,.Ltd
Category: otc | Type: HUMAN OTC DRUG LABEL
Date: 20210328

ACTIVE INGREDIENTS: ISOPROPYL ALCOHOL 75 mL/100 mL
INACTIVE INGREDIENTS: SODIUM CITRATE; PHENOXYETHANOL; WATER; GLYCERIN; ALOE; POLYAMINOPROPYL BIGUANIDE; .ALPHA.-TOCOPHEROL; PROPYLENE GLYCOL

ACTIVE INGREDIENT

lsopropyl Alcohol 75%

WARNINGS

For externial use only

Do not use if you are allergic to any of the ingredients

When using this product, do not get into eyes.lf contact occurs, rinse thoroughly with water.

Stop use and ask a doctor if irritation or rash develops and continues for more than 72 hours.

Keep out of reach of children. lf swallowed, get medical help or contact a Poison Control Center right away.

Directions

Adults and children 2 years & older:
Apply to hands
Ailow to dry without wiping
children under 2 years:
Ask a doctor before use

PURPOSE

Antiseptic

INACTIVE INGREDIENT

Water,Aloe Extract,VitaminE, Polyaminopropyl BiguanidePropylene glycol, Glycerin, Phenoxyethanol,Sodium Citrate

INDICATIONS AND USAGE

Help reduce bacteriathat potentially can cause disease.